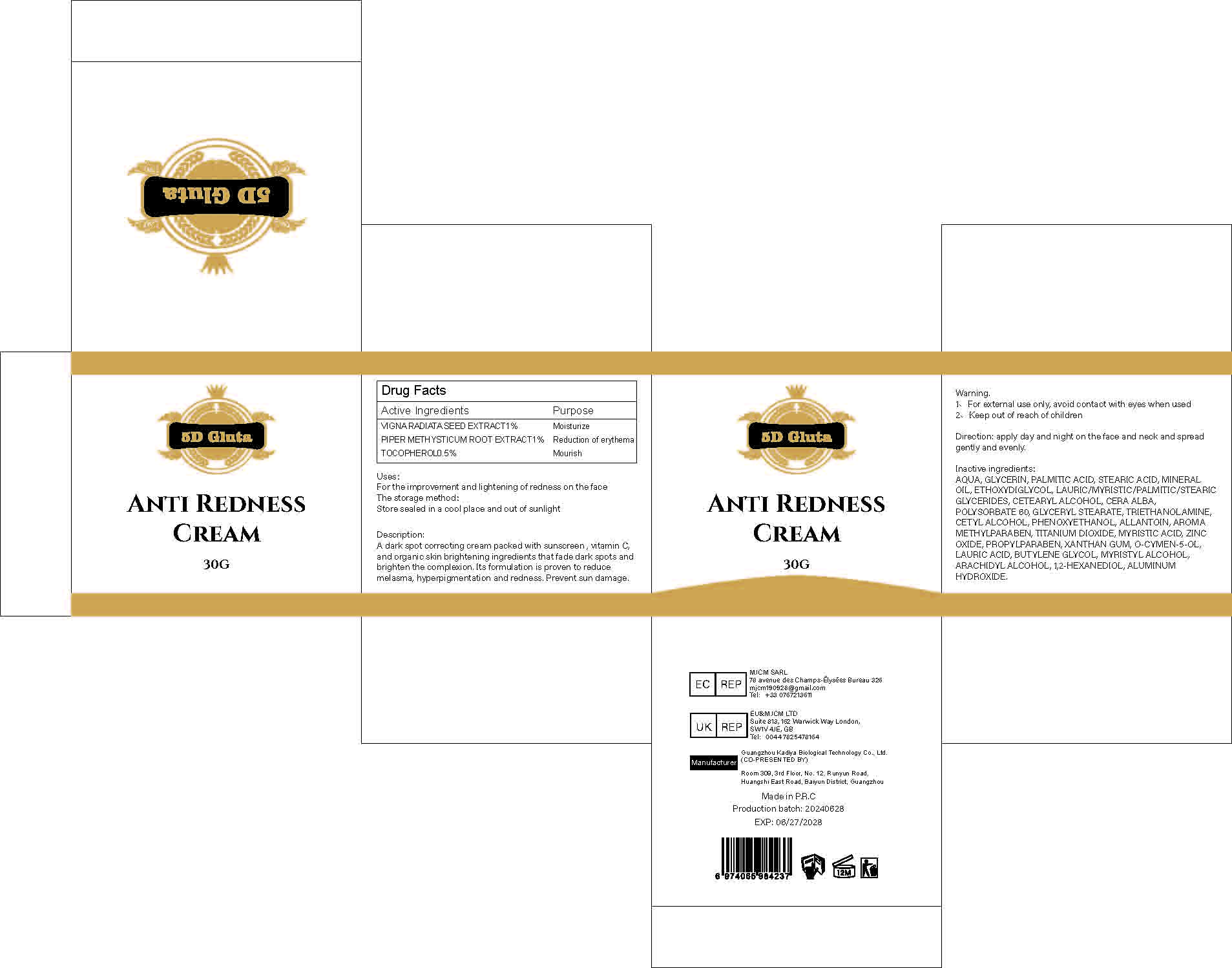 DRUG LABEL: Anti Redness Cream
NDC: 84423-022 | Form: EMULSION
Manufacturer: Guangzhou Kadiya Biotechnology Co., Ltd.
Category: otc | Type: HUMAN OTC DRUG LABEL
Date: 20240723

ACTIVE INGREDIENTS: PIPER METHYSTICUM ROOT 0.3 mg/30 mL; TOCOPHEROL 0.15 mg/30 mL; MUNG BEAN 0.3 mg/30 mL
INACTIVE INGREDIENTS: MINERAL OIL; GLYCERIN; DIETHYLENE GLYCOL MONOETHYL ETHER; PHENOXYETHANOL; ZINC OXIDE; PALMITIC ACID; MYRISTIC ACID; STEARIC ACID; CETOSTEARYL ALCOHOL; GLYCERYL MONOSTEARATE; LAURIC ACID; METHYLPARABEN; WHITE WAX; O-CYMEN-5-OL; MYRISTYL ALCOHOL; ARACHIDYL ALCOHOL; 1,2-HEXANEDIOL; WATER; ALLANTOIN; PROPYLPARABEN; BUTYLENE GLYCOL; ALUMINUM HYDROXIDE; POLYSORBATE 60; TITANIUM DIOXIDE; XANTHAN GUM; TROLAMINE; CETYL ALCOHOL

Uses：
For the improvement and lightening of redness on the face

INACTIVE INGREDIENT

AQUA、GLYCERIN、PALMITIC ACID、STEARIC ACID、MINERAL OIL、ETHOXYDIGLYCOL、LAURIC/MYRISTIC/PALMITIC/STEARIC GLYCERIDES、CETEARYL ALCOHOL、CERA ALBA、POLYSORBATE 60、GLYCERYL STEARATE、TRIETHANOLAMINE、CETYL ALCOHOL、PHENOXYETHANOL、ALLANTOIN、AROMA
METHYLPARABEN、TITANIUM DIOXIDE、MYRISTIC ACID、ZINC OXIDE、PROPYLPARABEN、XANTHAN GUM、O-CYMEN-5-OL、LAURIC ACID、BUTYLENE GLYCOL、MYRISTYL ALCOHOL、ARACHIDYL ALCOHOL、1,2-HEXANEDIOL、ALUMINUM HYDROXIDE

Warning.
1、For external use only, avoid contact with eyes when used
2、Keep out of reach of children

INDICATIONS AND USAGE

apply day and night on the face and neck and spread gently and evenly.

KEEP OUT OF REACH OF CHILDREN SECTION

ACTIVE INGREDIENT

VIGNA RADIATA SEED EXTRACT 1%
PIPER METHYSTICUM ROOT EXTRACT 1%
TOCOPHEROL 0.5%

DOSAGE AND ADMINISTRATION

A dark spot correcting cream packed with sunscreen, vitamin C, and organic skin brightening ingredients that fade dark spots and brighten the complexion. Its formulation is proven to reduce melasma, hyperpigmentation and redness. Prevent sun damage.

Drug Facts
Active Ingredients
VIGNA RADIATA SEED EXTRACT 1%
PIPER METHYSTICUM ROOT EXTRACT 1%
TOCOPHEROL 0.5%
Uses：
For the improvement and lightening of redness on the face
Indications: For the improvement and lightening of redness on the face
The storage method：
Store sealed in a cool place and out of sunlight
Warning.
1、For external use only, avoid contact with eyes when used
2、Keep out of reach of children
Inactive ingredients：
AQUA、GLYCERIN、PALMITIC ACID、STEARIC ACID、MINERAL OIL、ETHOXYDIGLYCOL、LAURIC/MYRISTIC/PALMITIC/STEARIC GLYCERIDES、CETEARYL ALCOHOL、CERA ALBA、POLYSORBATE 60、GLYCERYL STEARATE、TRIETHANOLAMINE、CETYL ALCOHOL、PHENOXYETHANOL、ALLANTOIN、AROMA
METHYLPARABEN、TITANIUM DIOXIDE、MYRISTIC ACID、ZINC OXIDE、PROPYLPARABEN、XANTHAN GUM、O-CYMEN-5-OL、LAURIC ACID、BUTYLENE GLYCOL、MYRISTYL ALCOHOL、ARACHIDYL ALCOHOL、1,2-HEXANEDIOL、ALUMINUM HYDROXIDE